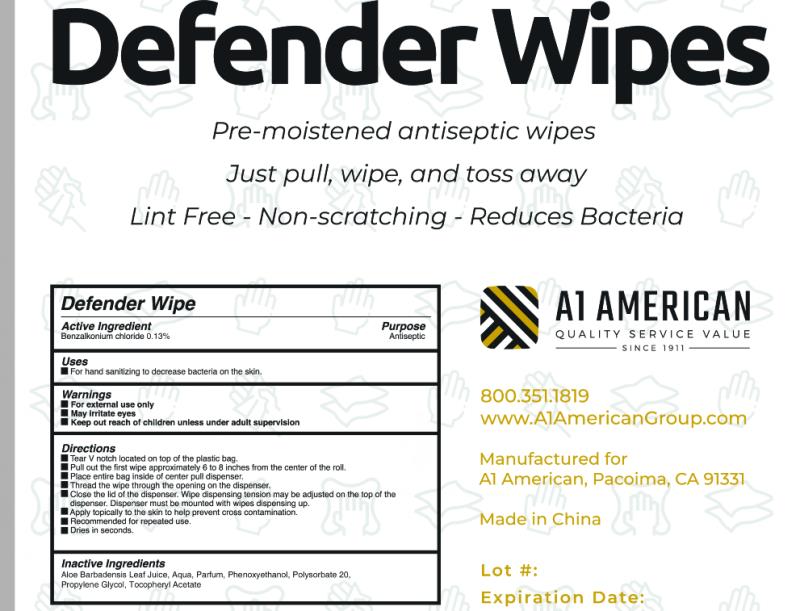 DRUG LABEL: Defender Wipe
NDC: 78411-002 | Form: SWAB
Manufacturer: Zhejiang Qirun Daily Necessities Co., Ltd.
Category: otc | Type: HUMAN OTC DRUG LABEL
Date: 20200728

ACTIVE INGREDIENTS: BENZALKONIUM CHLORIDE 0.13 g/100 g
INACTIVE INGREDIENTS: WATER; POLYSORBATE 20; PROPYLENE GLYCOL; PHENOXYETHANOL; .ALPHA.-TOCOPHEROL ACETATE

78411-002 defender wipes 0.13% BENZALKONIUM CHLORIDE

Active Ingredient

Benzalkonium Chloride 0.13%

Purpose

Antiseptic

USE

For hand sanitizing to decrease bacteria on the skin.

Warning

For external use only

May irritate eyes

Keep out reach of children unless under adult supervision

Keep out of reach of children unless under adult supervision

Directions

Tear V notch located on top of the plastic bag.
Pull out the first wipe approoirmately 6 to 8 inches from the center of the rol.
Place entire bag inside of center pull dispenser,
Thread the wipe through the opening on the dispenser,
Closo the id of the disponser. Wipe dispensing tension may be adjusted on tho top of
dispenser. Dispenser must be mounted with wipes desponsing up.
Apply topically to the skin to help prevent cross contamination.
Recommended for repeated use.
Dries in seconds.

Inactive ingredients

Aloe Barbadensis Leaf Juice, Aqua,Parfum, Phenoxyethanol, Propylene Glycol, Polysorbate 20,Tocopheryl Acetate